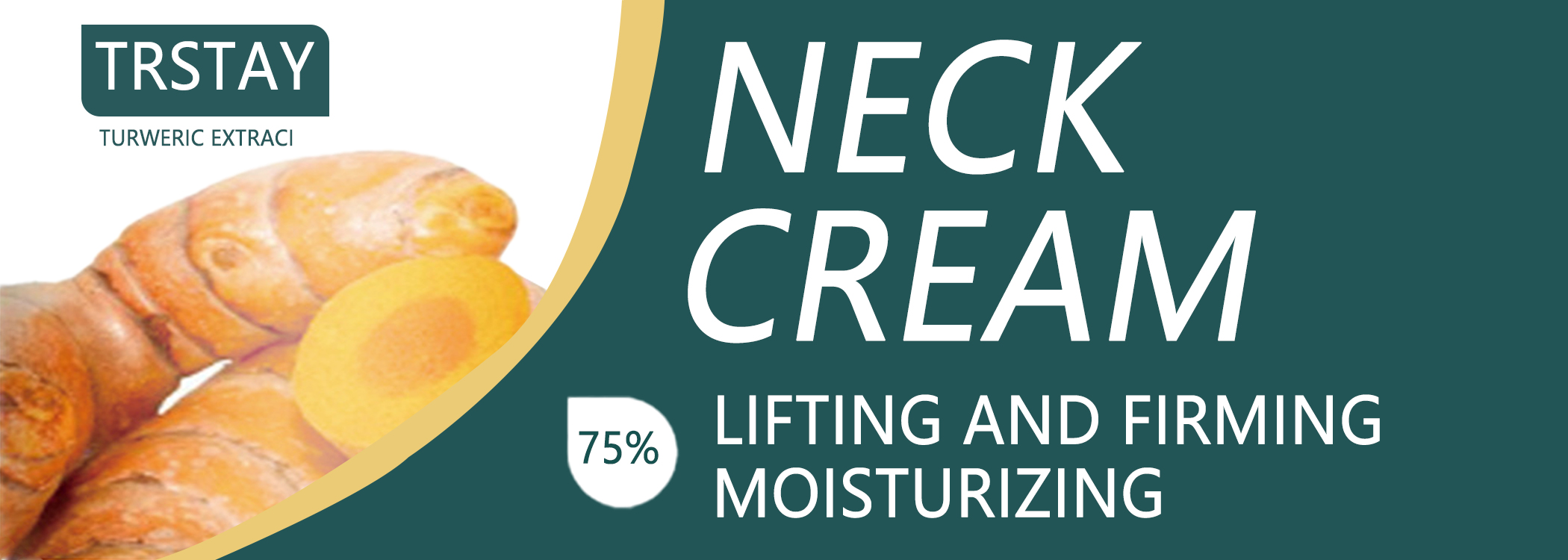 DRUG LABEL: Neck Cream
NDC: 84525-240 | Form: CREAM
Manufacturer: Yiwu Xinqian E  Commerce Co Ltd
Category: otc | Type: HUMAN OTC DRUG LABEL
Date: 20241031

ACTIVE INGREDIENTS: NIACINAMIDE 5 g/100 g
INACTIVE INGREDIENTS: CHLORPHENESIN; PALMITOYL TRIPEPTIDE-1; SESAME OIL; PALMITOYL PENTAPEPTIDE-4; GLYCERIN

COMPONENTS

Salicylic acid 2%

PURPOSE

wart remover

INDICATIONS AND USAGE

wart remover

DOSAGE AND ADMINISTRATION

For external use only.

WARNINGS

Forevemaluseony Avoid coniac wth eves li coniac ocus nse ihorouthly wt waier Keep out ofreach oi chidrenifvou ale preanant.nursing. otiaveanyunderving medca condion.consutyou healthcare provider before using the product

DO NOT USE

Discontinue use if any irritation or adverse reaction occurs

When using this product, avoid contact with eyes. lf contact occurs, rinse thoroughly with waterDiscontinue use if any irritation or adverse reaction occurs.

STOP USE

on broken or irritated scalp

INACTIVE INGREDIENT

Acrylates copolymer, Ethyl acetate